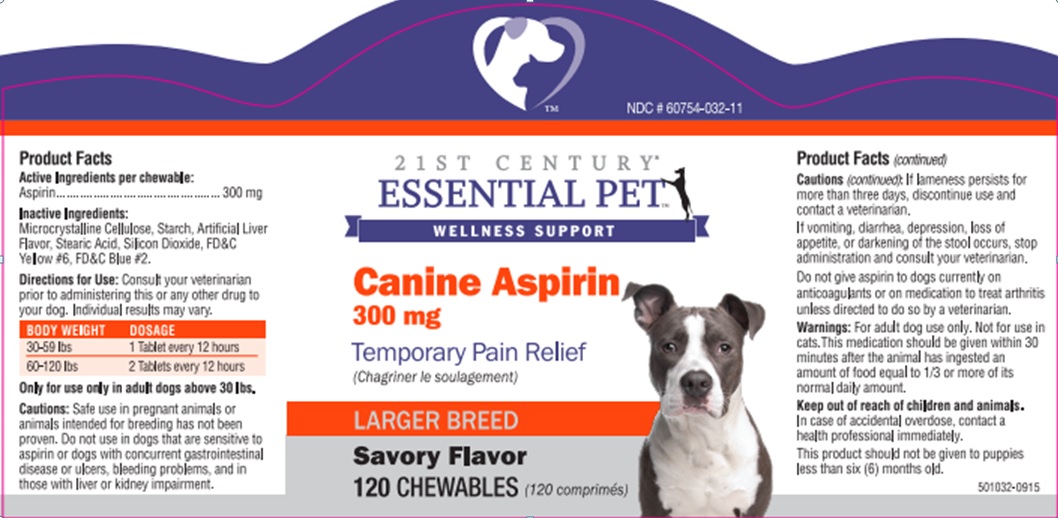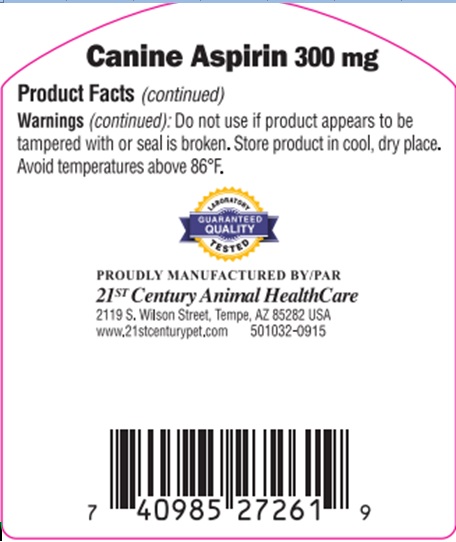 DRUG LABEL: Canine Aspirin
NDC: 60754-032 | Form: TABLET, CHEWABLE
Manufacturer: Twenty-First Century Healthcare Fund, L.L.C.
Category: animal | Type: OTC ANIMAL DRUG LABEL
Date: 20181227

ACTIVE INGREDIENTS: ASPIRIN 300 mg/1 1
INACTIVE INGREDIENTS: CELLULOSE, MICROCRYSTALLINE; STEARIC ACID; SILICON DIOXIDE; FD&C YELLOW NO. 6; FD&C BLUE NO. 2

Canine Aspirin

Active Ingredients per Chewable:

Aspirin ...... 300 mg

Inactive Ingredients:

Microcrystalline Cellulose, Starch, Artificial Liver Flavor, Stearic Acid, Silicon Dioxide, FDandC Yellow 6, FDandC Blue 2.

Directions for Use:

Consult your veterinarian prior to administering this or any other drug to your dog. Individual results may vary.

BODY WEIGHT | DOSAGE
30-59 lbs | 1 Tablet every 12 hours
60-120 lbs | 2 Tablets every 12 hours

Only for use in adult dogs above 30 lbs.

Cautions:

Safe use in pregnant animals or animals intended for breeding has not been proven. Do not use in dogs that are sensitive to aspirin or dogs with concurrent gastrointestinal disease or ulcers, bleeding problems, and in those with liver or kidney impairment.

If lameness persists for more than three days, discontinue use and contact a veterinarian.

If vomiting, diarrhea, depression or loss of appetite or darkening of the stool occurs, stop administration and consult your veterinarian.

Do not give aspirin to dogs currently on anticoagulants or on medication to treat arthritis unless directed to do so by a veterinarian.

Warnings:

For dog use only. Not for use in cats.

This medication should be given within 30 minutes after the animal has ingested an amount of food equal to 1/3 or more of its normal daily amount.

Keep out of reach of children and animals.

In case of accidental overdose, contact a health professional immediately.

This product should not be given to puppies less than six (6) months old.

Do not use

if product appears to be tampered with or seal is broken. Store product in cool, dry place. Avoid temperatures above 86 degrees F.